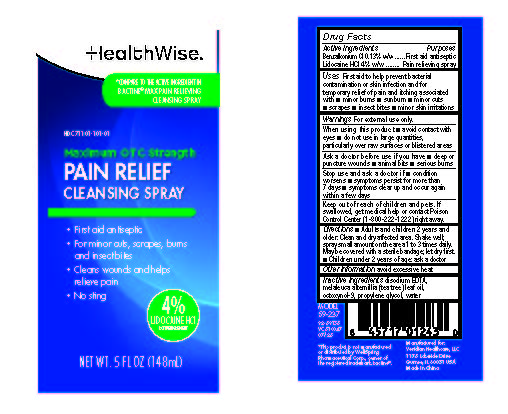 DRUG LABEL: HealthWise Lidocaine Cleansing
NDC: 71101-101 | Form: LIQUID
Manufacturer: Veridian Healthcare
Category: otc | Type: HUMAN OTC DRUG LABEL
Date: 20250812

ACTIVE INGREDIENTS: BENZALKONIUM CHLORIDE 0.13 g/100 mL; LIDOCAINE HYDROCHLORIDE 4 g/100 mL
INACTIVE INGREDIENTS: EDETATE DISODIUM; PROPYLENE GLYCOL; WATER; OCTOXYNOL 9; MELALEUCA ALTERNIFOLIA (TEA TREE) LEAF OIL

HealthWise 4% Lidocaine Cleansing Spray

Drug Facts

Benzalkonium CL Lidocaine HCl

Active ingredients | Purpose
Benzalkonium Cl 0.13% w/w | First aid antiseptic
Lidocaine HCl 4% w/w | Pain relieving spray

Uses

first aid to help prevent bacterial contamination or skin infection, and for temporary relief of pain and itching associated with:

- minor burns
- sunburn
- minor cuts
- scrapes
- insect bites
- minor skin irritations

Warnings

For external use only

Ask a doctor before use if you have

- deep or puncture wounds
- animal bites
- serious burns

When using this product

- avoid contact with eyes
- do not use in large quantities, particularly over raw surfaces or blistered areas

Stop use and ask a doctor if

- condition worsens
- symptoms persist for more than 7 days,
- symptoms or clear up and occur again within a few days

Keep out of reach of children.If swallowed, get medical help or contact a Poison Control Center (1-800-222-1222) right away.

Directions

- adults and children 2 years and older: clean and dry affected area. Shake well; spray small amount on the area 1-3 times daily. May be covered with a sterile bandage (let dry first)
- children under 2 years, ask a doctor

Other information

avoid excessive heat

Inactive ingredients

edetate disodium, fragrances, propylene glycol, purified water